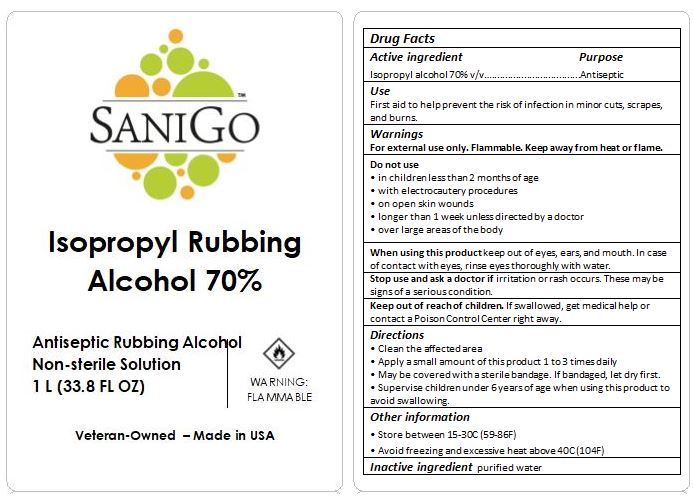 DRUG LABEL: Sanigo Rubbing Alcohol
NDC: 77979-200 | Form: LIQUID
Manufacturer: KPaul
Category: otc | Type: HUMAN OTC DRUG LABEL
Date: 20220904

ACTIVE INGREDIENTS: ISOPROPYL ALCOHOL 70 mL/100 mL
INACTIVE INGREDIENTS: WATER 30 mL/100 mL

Active Ingredient(s)

Isopropyl Alcohol 70% v/v. Purpose: Antiseptic

Purpose

Antiseptic, Rubbing Alcohol

Use

First aid to help prevent the risk of infection in minor cuts, scrapes, and burns.

Warnings

For external use only. Flammable. Keep away from heat or flame

Do not use

- in children less than 2 months of age
- with electrocautery procedures
- on open skin wounds
- longer than 1 week unless directed by a doctor
- over large areas of the body

When using this product keep out of eyes, ears, and mouth. In case of contact with eyes, rinse eyes thoroughly with water.

Stop use and ask a doctor if irritation or rash occurs. These may be signs of a serious condition.

Keep out of reach of children. If swallowed, get medical help or contact a Poison Control Center right away.

Directions

- Clean the affacted area
- Apply a small amount of this product 1 to 3 times daily.
- May be covered with a sterile bandage. If bandaged, let dry first.
- Supervise children under 6 years of age when using this product to avoid swallowing.

Other information

- Store between 15-30C (59-86F)
- Avoid freezing and excessive heat above 40C (104F)

Inactive ingredients

purified water